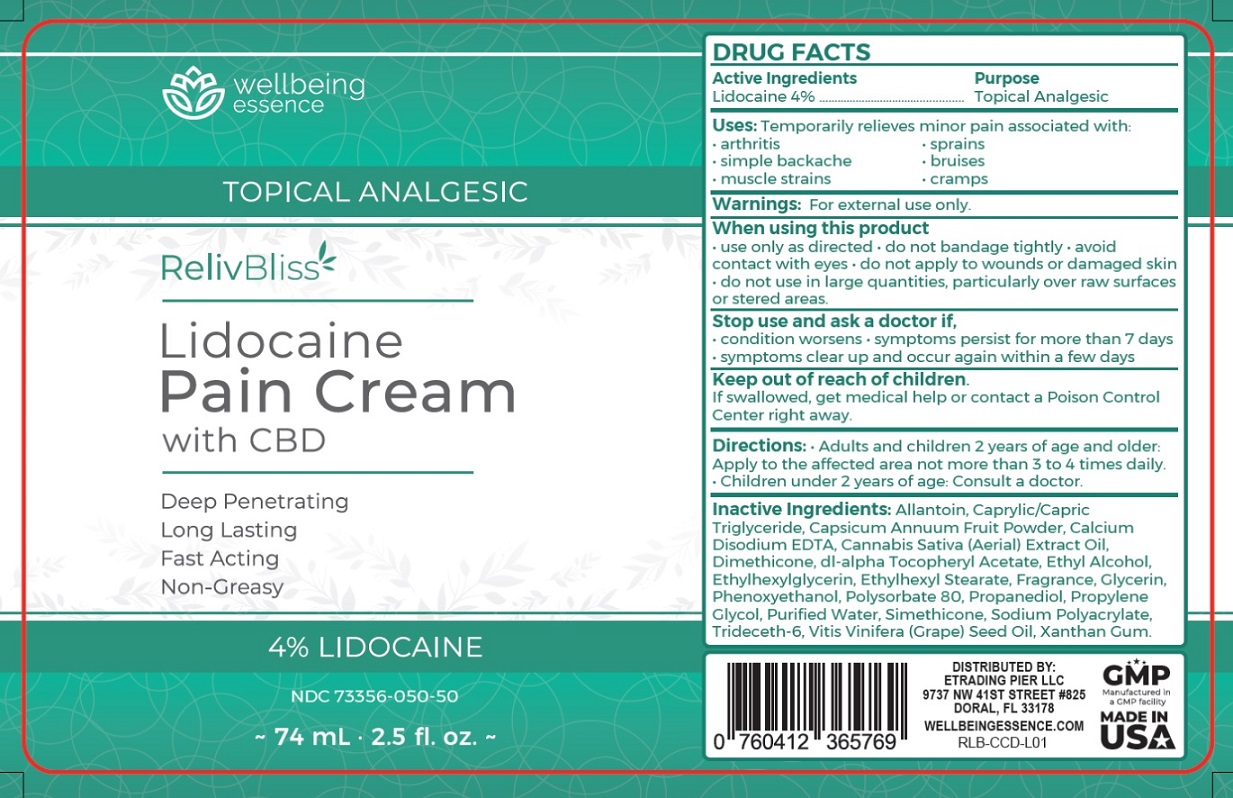 DRUG LABEL: RelivBliss
NDC: 73356-050 | Form: CREAM
Manufacturer: Etrading Pier Llc
Category: otc | Type: HUMAN OTC DRUG LABEL
Date: 20191021

ACTIVE INGREDIENTS: LIDOCAINE HYDROCHLORIDE 4 g/100 mL
INACTIVE INGREDIENTS: ALLANTOIN; MEDIUM-CHAIN TRIGLYCERIDES; PAPRIKA; EDETATE CALCIUM DISODIUM ANHYDROUS; CANNABIS SATIVA SUBSP. SATIVA FLOWERING TOP; DIMETHICONE; .ALPHA.-TOCOPHEROL ACETATE, DL-; ALCOHOL; ETHYLHEXYLGLYCERIN; ETHYLHEXYL STEARATE; GLYCERIN; PHENOXYETHANOL; POLYSORBATE 80; PROPANEDIOL; PROPYLENE GLYCOL; WATER; SILICON DIOXIDE; SODIUM POLYACRYLATE (8000 MW); TRIDECETH-6; GRAPE SEED OIL; XANTHAN GUM

RelivBliss Lidocaine Pain Cream with CBD

Active Ingredients

Lidocaine 4%

Purpose

Topical Analgesic

INDICATIONS AND USAGE

Uses: Temporarily relieves minor pain associated with:
• arthritis • sprains
• simple backache • bruises
• muscle strains • cramps

Warnings: For external use only.

When using this product
• use only as directed • do not bandage tightly • avoid contact with eyes • do not apply to wounds or damaged skin
• do not use in large quantities, particularly over raw surfaces or stered areas.

Stop use and ask a doctor if,
• condition worsens • symptoms persist for more than 7 days
• symptoms clear up and occur again within a few days

Keep out of reach of children.
If swallowed, get medical help or contact a Poison Control Center right away.

DOSAGE AND ADMINISTRATION

Directions: • Adults and children 2 years of age and older:
Apply to the affected area not more than 3 to 4 times daily.
• Children under 2 years of age: Consult a doctor.

INACTIVE INGREDIENT

Inactive Ingredients: Allantoin, Caprylic/Capric Triglyceride, Capsicum Annuum Fruit Powder, Calcium Disodium EDTA, Cannabis Sativa (Aerial) Extract Oil, Dimethicone, dl-alpha Tocopheryl Acetate, Ethyl Alcohol, Ethylhexylglycerin, Ethylhexyl Stearate, Fragrance, Glycerin, Phenoxyethanol, Polysorbate 80, Propanediol, Propylene Glycol, Purified Water, Simethicone, Sodium Polyacrylate, Trideceth-6, Vitis Vinifera (Grape) Seed Oil, Xanthan Gum.

Deep Penetrating
Long Lasting
Fast Acting
Non-Greasy

DISTRIBUTED BY:
ETRADING PIER LLC
9737 NW 41ST STREET #825
DORAL, FL 33178
WELLBEINGESSENCE.COM

Manufactured in a GMP facility

Made in USA